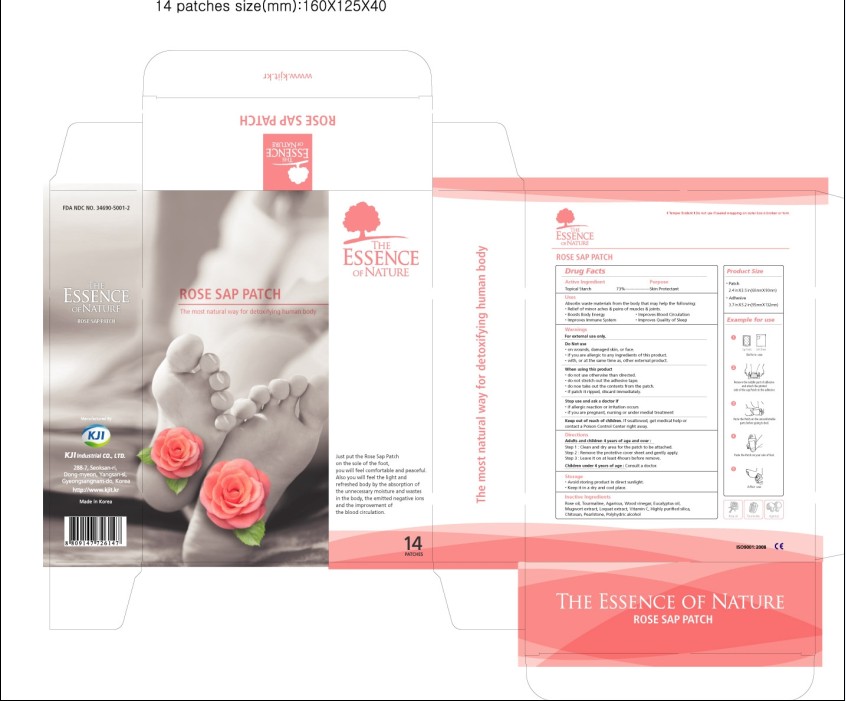 DRUG LABEL: Rose Sap Patch
NDC: 34690-5001 | Form: POULTICE
Manufacturer: KJI Industrial Co Ltd
Category: otc | Type: HUMAN OTC DRUG LABEL
Date: 20100111

ACTIVE INGREDIENTS: STARCH, CORN 2.92 g/4 g

Warnings: For external use only

Do Not Use
- on wounds, damaged skin or face
- if you are allergic to any ingredients of this product
- with or at the same time as other external product

When using this product
- do not use otherwise than directed
- do not stretch out the adhesive tape
- do not take out the contents from the patch
- if patch is ripped, discard immediately

Stop use and ask a doctor if
- if allergic reaction or irritation occurs
- if you are pregnant, nursing or under medical treatment

Keep out of reach of children
- if swallowed, get medical help or contact a Poison Control Center right away

Directions
Adults and children 4 years of age and over:
Step 1: Clean and dry area for the patch to be attached
Step 2: Remove the protective cover sheet and gently apply
Step 3: Leave it on at least 4 hours before removal
Children under 4 years of age: Consult a doctor

Storage
- Avoid storing product in direct sunlight
- Keep it in a dry and cool place

Active Ingredient:
Topical Starch 73% ........................... Skin Protectant

Inactive Ingredients:
Wood Vinegar, Tourmaline, Agaricus, Eucalyptus oil, Mugwort extract, Loquat extract, Vitamin C, Chitosan, Highly purified Silica, Pearlstone, Polyhydric alcohol, Rose oil